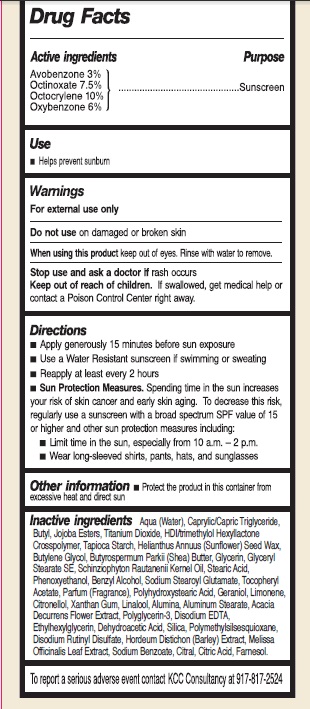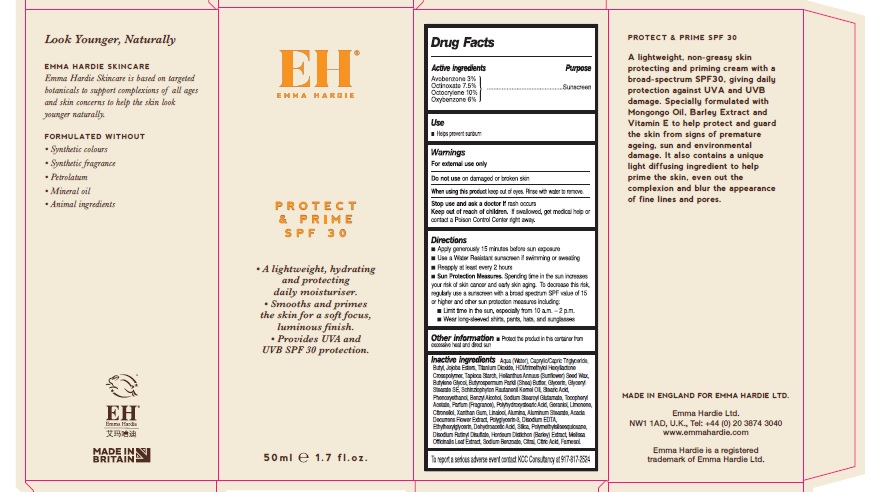 DRUG LABEL: Protect and Prime Broad Spectrum SPF30
NDC: 70453-001 | Form: CREAM
Manufacturer: Emma Hardie Ltd
Category: otc | Type: HUMAN OTC DRUG LABEL
Date: 20231110

ACTIVE INGREDIENTS: AVOBENZONE 30 mg/1 mL; OCTINOXATE 75 mg/1 mL; OCTOCRYLENE 100 mg/1 mL; OXYBENZONE 60 mg/1 mL
INACTIVE INGREDIENTS: WATER; MEDIUM-CHAIN TRIGLYCERIDES; SIMMONDSIA CHINENSIS SEED WAX; HELIANTHUS ANNUUS SEED WAX; HEXAMETHYLENE DIISOCYANATE/TRIMETHYLOL HEXYLLACTONE CROSSPOLYMER; SCHINZIOPHYTON RAUTANENII SEED OIL; SHEA BUTTER; STEARIC ACID; GLYCERIN; 1,4-BUTANEDIOL MONOSTEARATE; PHENOXYETHANOL; BENZYL ALCOHOL; SODIUM STEAROYL GLUTAMATE; .ALPHA.-TOCOPHEROL ACETATE; GERANIOL; .BETA.-CITRONELLOL, (R)-; XANTHAN GUM; LINALOOL, (+/-)-; ALUMINUM OXIDE; ALUMINUM STEARATE; EDETATE DISODIUM; ETHYLHEXYLGLYCERIN; DEHYDROACETIC ACID; SILICON DIOXIDE; SODIUM STEARATE; DISODIUM RUTINYL DISULFATE; BARLEY; MELISSA OFFICINALIS LEAF; SODIUM BENZOATE; CITRAL; CITRIC ACID MONOHYDRATE; FARNESOL; TITANIUM DIOXIDE

Protect & Prime Broad Spectrum SPF30

Active ingredients

Avobenzone 3%

Octinoxate 7.5%

Octocrylene 10%

Oxybenzone 6%

Purpose

Sunscreen

Use

- Helps prevent sunburn

Warnings

For external use only

Do not use

on damaged or broken skin

When using this product

keep out of eyes. Rinse with water to remove.

Stop use and ask a doctor if

rash occurs

Keep out of reach of children.

If swallowed, get medical help or contact a Poison Control Center right away.

Directions

- Apply generously 15 minutes before sun exposure
- Use a Water Resistant sunscreen if swimming or sweating
- Reapply at least every 2 hours
- Spending time in the sun increases your risk of skin cancer and early skin aging. To decrease this risk, regularly use a sunscreen with a broad spectrum SPF value of 15 or higher and other sun protection measures including: Sun Protection Measures.
- Limit time in the sun, especially from 10 a.m. - 2 p.m.
- Wear long-sleeved shirts, pants, hats, and sunglasses

Other information

- Protect the product in this container from excessive heat and direct sun

Inactive ingredients

Water (Aqua), caprylic/capric triglyceride, Green Wattle (Acacia Decurrens)/Jojoba (Simmondsia Chinensis)/Sunflower (Helianthis Annus) Seed Wax/Polyglyceryl-3 Esters, HDI/Trimethylol Hexyllactone Crosspolymer, Tapioca Starch, Manketti (Schinziophyton Rautaneii) Kernel Oil, Shea Butter (Vitellaria Paradoxa), Stearic Acid, Glycerin, Butylene Glycol Stearate SE, Phenoxyethanol, Benzyl Alcohol, Sodium Stearoyl Glutamate, Tocopheryl Acetate, Fragrance (Parfum), Polyhydroxystearic Acid, Geraniol, Limonene, Citronellol, Xanthan Gum, Linalool, Alumina, Aluminum Stearate, Disodium EDTA, Ethylhexylglycerin, Dehydroacetic Acid, Silica, Sodium Stearate, Polymethylsilsesquioxane, Disodium Rutinyl Disulfate, Barley (Hordeum Districhon) Extract, Lemon Balm (Melissa Officinalis) Leaf Extract, Sodium Benzoate, Citral, Citric Acid, Farnesol, Titanium Dioxide (CI 77891)